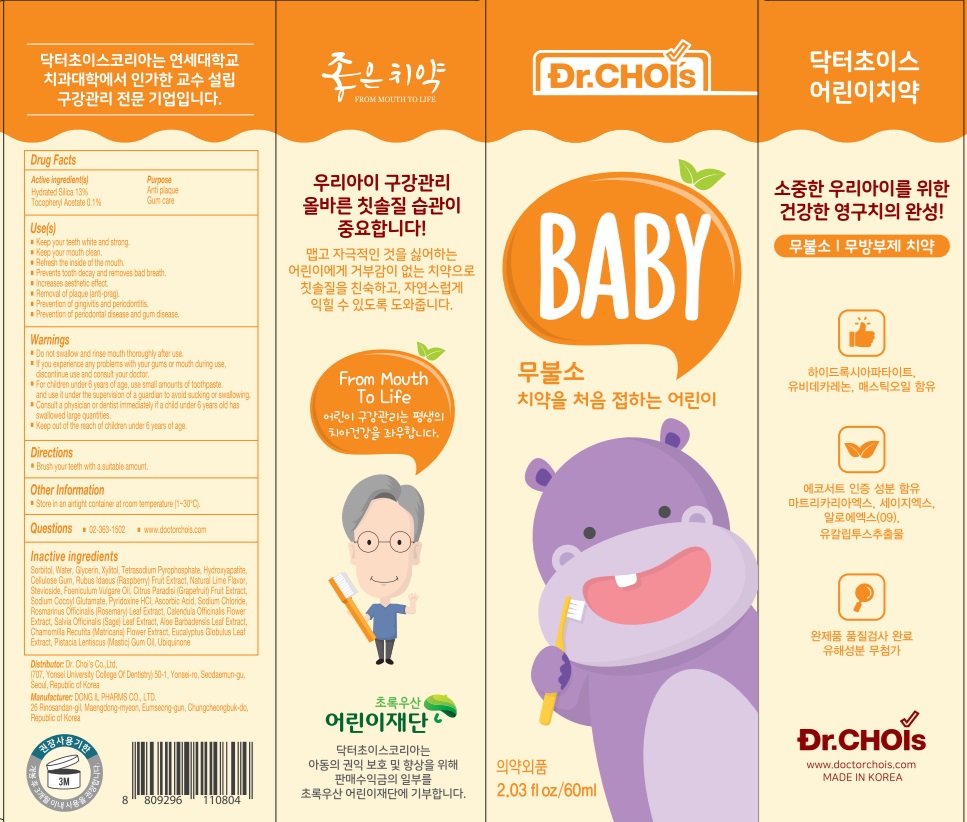 DRUG LABEL: DR.CHOIS TOOTHPASTE STEP ONE BABIES
NDC: 73666-0530 | Form: PASTE, DENTIFRICE
Manufacturer: Doctor Choi`s Korea Co., LTD.
Category: otc | Type: HUMAN OTC DRUG LABEL
Date: 20241114

ACTIVE INGREDIENTS: HYDRATED SILICA 13 g/100 g; .ALPHA.-TOCOPHEROL ACETATE 0.1 g/100 g
INACTIVE INGREDIENTS: SORBITOL; WATER; GLYCERIN

ACTIVE INGREDIENTS

Hydrated Silica 13%
Tocopheryl Acetate 0.1%

PURPOSE

Anti plaque
Gum care

Uses

■ Keep your teeth white and strong.
■ Keep your mouth clean.
■ Refresh the inside of the mouth.
■ Prevents tooth decay and removes bad breath.
■ Increases aesthetic effect.
■ Removal of plaque (anti-prag)
■ Prevention of gingivitis and periodontitis
■ Prevention of periodontal disease and gum disease.

WARNINGS

■ Do not swallow and rinse mouth thoroughly after use
■ If you experience any problems with your gums or mouth during use,
discontinue use and consult your doctor.
■ For children under 6 years of age, use small amounts of toothpaste. And use it
under the supervision of a guardian to avoid sucking or swallowing.
■ Consult a physician or dentist immediately if a child under 6 years old has
swallowed large quantities.
■ Keep out of the reach of children under 6 years of age.

KEEP OUT OF REACH OF CHILDREN

■ Keep out of the reach of children under 6 years of age.

Directions

■ Brush your teeth with a suitable amount

Other Information

■ Store in an airtight container at room temperature (1~30℃)

Questions

■ 02-363-1502
■ www.doctorchois.com

INACTIVE INGREDIENTS

Sorbitol, Water, Glycerin, Xylitol, Tetrasodium Pyrophosphate, Hydroxyapatite, Cellulose Gum, Rubus Idaeus (Raspberry) Fruit Extract, Lime Flavor, Stevioside, Foeniculum Vulgare Oil, Citrus Paradisi (Grapefruit) Fruit Extract, Sodium Cocoyl Glutamate, Pyridoxine HCl, Ascorbic Acid,
Sodium Chloride, "Rosmarinus Officinalis (Rosemary) Leaf Extract", Calendula Officinalis Flower Extract, Salvia Officinalis (Sage) Leaf Extract, Aloe Barbadensis Leaf Extract, Chamomilla Recutita (Matricaria) Flower Extract, Eucalyptus Globulus Leaf Extract, Pistacia Lentiscus (Mastic) Gum Oil, Ubiquinone